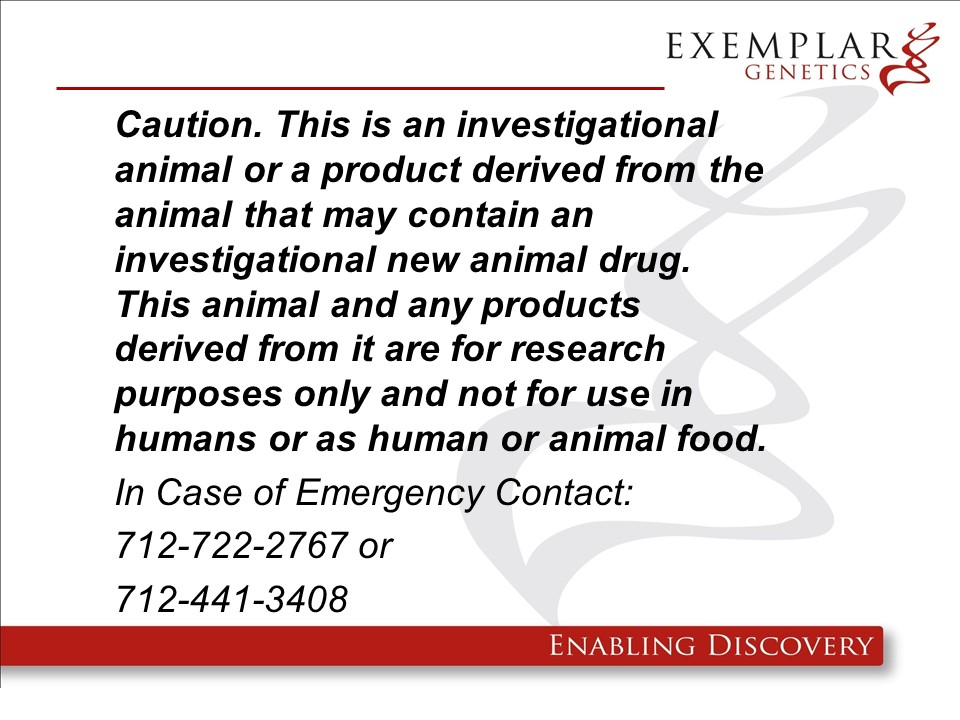 DRUG LABEL: ExeGen LDLR Miniswine
NDC: 86093-1901 | Form: NOT APPLICABLE
Manufacturer: Exemplar Genetics, LLC
Category: other | Type: INTENTIONAL ANIMAL GENOMIC ALTERATION LABEL
Date: 20250521

ACTIVE INGREDIENTS: YUCATAN MINIATURE PIG LDLR GENE DISRUPTED BY A LDLR-NEO RDNA CONSTRUCT IN EXON 4   1 [arb'U]/1 [arb'U]

pLDLR-Neo in miniswine

ExeGen LDLR miniswine are genetically engineered yucatan miniature swine containing the rDNA contruct pLDLR-Neo which exhibit similar phenotypes to human patients in which the same LDLR gene is non-funtional. Phenotypes include severely elevated serum cholesterol (total cholesterol and LDL) and atherocsclerosis. These pigs are intended to be used as large animla models of human disease. We will not be requesting a food use authorization and the carcasses and all materials feneated from these animals will be destroyed by incineration.

Product Definition: A specific lin of Yucatan miniatue pigs (Sus scrofa domesticus), indlucing both homozygous and heterozygous offspring resulting from a heterozygous founder, in which the LDLR (low-density lipoprotein receptor) gene has been disrupted by the homologuous recombination of a single copy of a pLDLR-Neo contruct in exon 4, for use in biomedical research.

Warning: this product is from a genetically engineered animal and may contain an investigational new animal drug. It is for research purposes only and not ro use in humans or as food/feed unless authorization has been granted by the US Food and Drug Administration. In case of emergency or release contact Exemplar Genetics at 712-722-2767 or 712-441-3408.